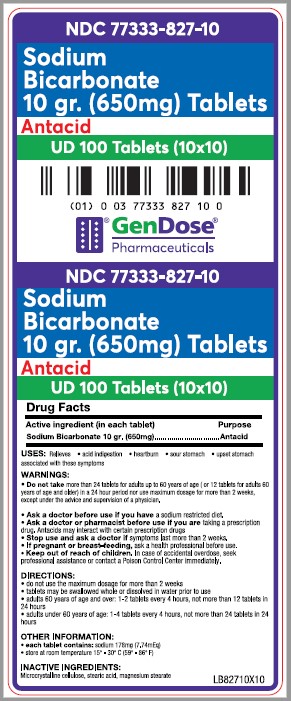 DRUG LABEL: Sodium Bicarbonate

NDC: 77333-827 | Form: TABLET
Manufacturer: Gendose Pharmaceuticals, LLC
Category: otc | Type: HUMAN OTC DRUG LABEL
Date: 20250702

ACTIVE INGREDIENTS: SODIUM BICARBONATE 650 mg/1 1
INACTIVE INGREDIENTS: MAGNESIUM STEARATE; MICROCRYSTALLINE CELLULOSE; STEARIC ACID

GENDOSE - Sodium Bicarbonate 10 gr (650 mg) TABLETS (77333-827)

Active ingredient (in each tablet)

Sodium bicarbonate 10 gr. (650 mg)

Purpose

Antacid

Uses

Relieves

- acid indigestion
- heartburn
- sour stomach
- upset stomach associated with these symptoms

WARNINGS

- DO NOT TAKE MORE THAN 24 TABLETS FOR ADULTS UP TO 60 YEARS OF AGE (0R 12 TABLETS FOR ADULTS 60 YEARS OF AGE AND OLDER) IN A 24 HOUR PERIOD NOR USE MAXIMUM DOSAGE FOR MORE THAN 2 WEEKS, EXCEPT UNDER THE ADVICE AND SUPERVISION OF A PHYSICIAN.
- ASK A DOCTOR BEFORE USE IF YOU HAVE A SODIUM RESTRICTED DIET.
- ASK A DOCTOR OR PHARMACIST BEFORE USE IF YOU ARE TAKING A PRESCRIPTION DRUG. ANTACIDS MAY INTERACT WITH CERTAIN PRESCRIPTION DRUGS.
- STOP USE AND ASK A DOCTOR IF SYMPTOMS LAST MORE THAN 2 WEEKS.
- IF PREGNANT OR BREAST-FEEDING, ASK A HEALTH PROFESSIONAL BEFORE USE.

- KEEP OUT OF REACH OF CHILDREN. IN CASE OF ACCIDENTAL OVERDOSE, SEEK PROFESSIONAL ASSISTANCE OR CONTACT A POISON CONTROL CENTER IMMEDIATELY.

DIRECTIONS

- DO NOT USE THE MAXIMUM DOSAGE FOR MORE THAN 2 WEEKS
- TABLETS MAY BE SWALLOWED WHOLE OR DISSOLVED IN WATER PRIOR TO USE
- ADULTS 60 YEARS OF AGE AND OVER: 1-2 TABLETS EVERY 4 HOURS, NOT MORE THAN 12 TABLETS IN 24 HOURS
- ADULTS UNDER 60 YEARS OF AGE: 1-4 TABLETS EVERY 4 HOURS, NOT MORE THAN 24 TABLETS IN 24 HOURS

OTHER INFORMATION

- each tablet contains : sodium 178 mg (7.74 mEq)
- store at room temperature 15°-30°C (59°-86°F)

INACTIVE INGREDIENTS

MICROCRYSTALLINE CELLULOSE, STEARIC ACID, MAGNESIUM STEARATE